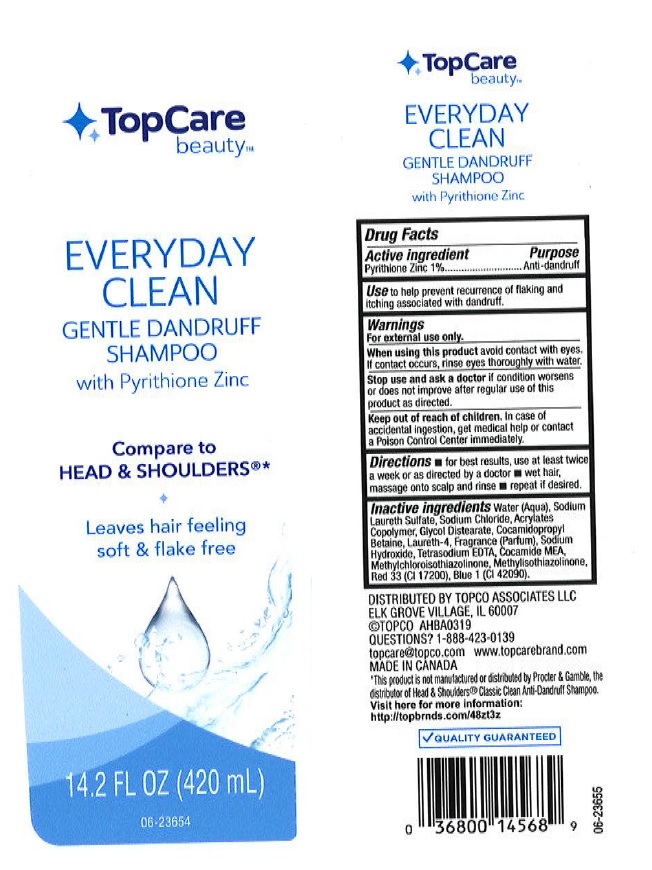 DRUG LABEL: Topcare Everyday Clean Dandruff
NDC: 36800-795 | Form: SHAMPOO
Manufacturer: Topco Associates LLC
Category: otc | Type: HUMAN OTC DRUG LABEL
Date: 20190930

ACTIVE INGREDIENTS: PYRITHIONE ZINC 10 mg/1 mL
INACTIVE INGREDIENTS: WATER; SODIUM LAURETH SULFATE; SODIUM CHLORIDE; METHACRYLIC ACID - METHYL METHACRYLATE COPOLYMER (1:1); GLYCOL DISTEARATE; COCAMIDOPROPYL BETAINE; LAURETH-4; SODIUM HYDROXIDE; EDETATE SODIUM; COCO MONOETHANOLAMIDE; METHYLCHLOROISOTHIAZOLINONE; METHYLISOTHIAZOLINONE; D&C RED NO. 33; FD&C BLUE NO. 1

Drug Facts

Active ingredient

Pyrithione Zinc 1%

Purpose

Antidandruff

Use

to help prevent recurrence of flaking and itching associated with dandruff.

Warnings

For external use only

When using this product

avoid contact with eyes. If contact occurs, rinse thoroughly with water.

Stop use and ask a doctor if

condition worsens or does not improve after regular use of this product as directed

Keep out of reach of children.

In case of accidental ingestion, get medical help or contact a Poison Control Center immediately.

Directions

- for best results, use at least twice a week or as directed by a doctor
- wet hair, massage onto scalp and rinse
- repeat if desired

Inactive ingredients

Water (Aqua), Sodium Laureth Sulfate, Sodium Chloride, Acrylates Copolymer, Glycol Distearate, Cocamidopropyl Betaine, Laureth-4, Fragrance (Parfum), Sodium Hydroxide, Tetrasodium EDTA, Cocamide MEA, Methylchloroisothiazolinone, Methylisothiazolinone, Red 33 (CI 17200), Blue 1 (CI 42090).